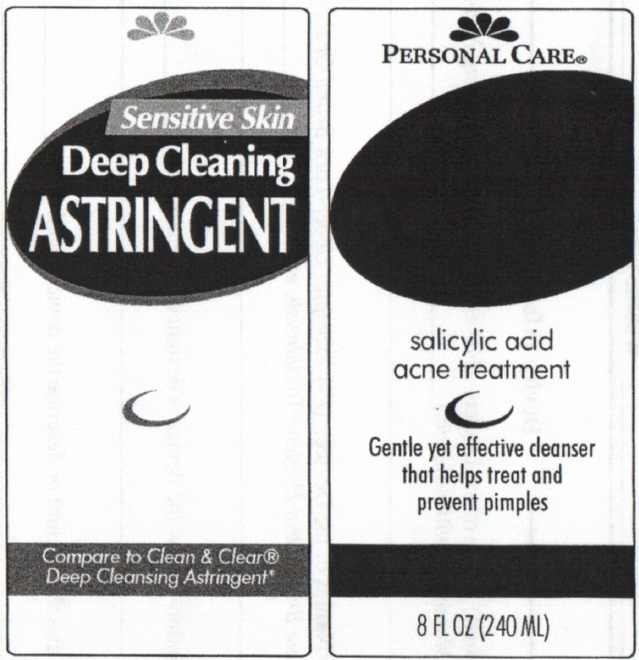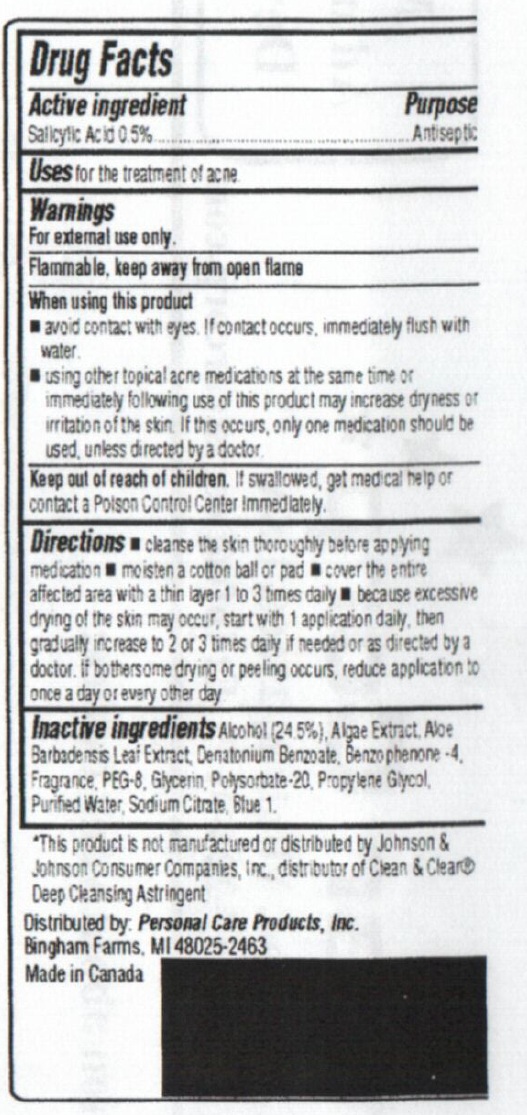 DRUG LABEL: Personal Care Sensitive Skin Deep Cleaning Astringent
NDC: 29500-7000 | Form: LIQUID
Manufacturer: Personal Care Products, LLC
Category: otc | Type: HUMAN OTC DRUG LABEL
Date: 20110125

ACTIVE INGREDIENTS: SALICYLIC ACID 0.5 mL/100 mL
INACTIVE INGREDIENTS: ALCOHOL; ALOE VERA LEAF; DENATONIUM BENZOATE; SULISOBENZONE; POLYOXYL 8 STEARATE; GLYCERIN; POLYSORBATE 20; PROPYLENE GLYCOL; WATER; SODIUM CITRATE; FD&C BLUE NO. 1

Personal Care Sensitive Skin Deep Cleaning Astringent

Active Ingredient

Salicylic Acid 0.5 percent

Purpose Antiseptic

INDICATIONS AND USAGE

Uses for the treatment of acne.

Warnings
For external use only.
Flammable, keep away from open flame

When using this product

avoid contact with eyes. If contact occurs, immediately flush with water

using other topical acne medications at the same time or immediately following use of this

product may increase dryness or irritation of the skin. If this occurs, only one medication should

be used, unless directed by a doctor.

Keep out of reach of children. If swallowed, get medical help or contact

a Poison Control Center immediately.

Directions

Cleanse the skin thoroughly before applying medication

Moisten a cotton ball or pad

Cover the entire affected area with a thin layer 1 to 3 times daily

Because excessive drying of the skin may occur, start with 1 application daily then gradually increase to 2 or 3 times daily if needed or as directed by a doctor.

If bothersome drying or peeling occurs, reduce application to once a day or every other day.

Inactive ingredients

Alcohol (24.5 percent), Algae Extract, Aloe Barbadensis Leaf Extract,

Denatonium Benzoate, Benzophenone-4, Fragrance, PEG-8,

Glycerin, Polysorbate-20, Propylene Glycol, Purified Water, Sodium Citrate, Blue 1

DESCRIPTION

This product is not manufactured or distributed by Johnson and Johnson Consumer

Companies, Inc., distributor of Clean and Clear Deep Cleansing Astringent

Distributed by: Personal Care Products, Inc.

Bingham Farms, MI 48025-2463

Made in Canada

PACKAGE LABEL

Personal Care

Sensitive Skin

Deep Cleaning Astringent

salicylic acid

acne treatment

Gentle yet effective cleanser

that helps

treat and prevent pimples

Compare to Clean and Clear

Deep Cleaning Astringent

8 FL OZ (240 ML)